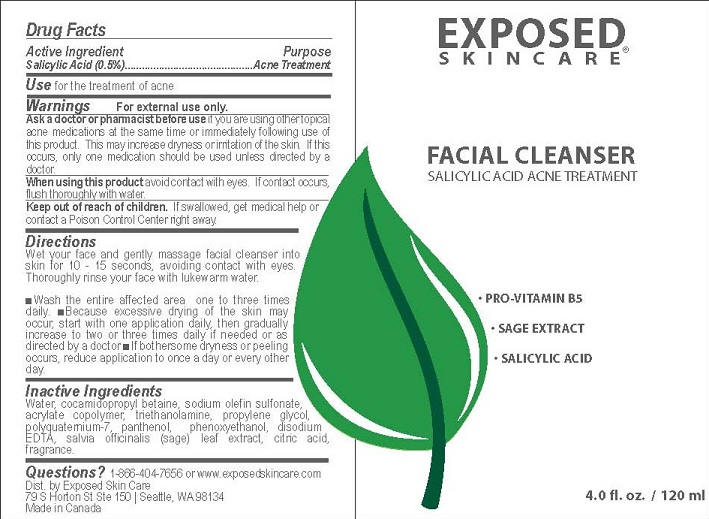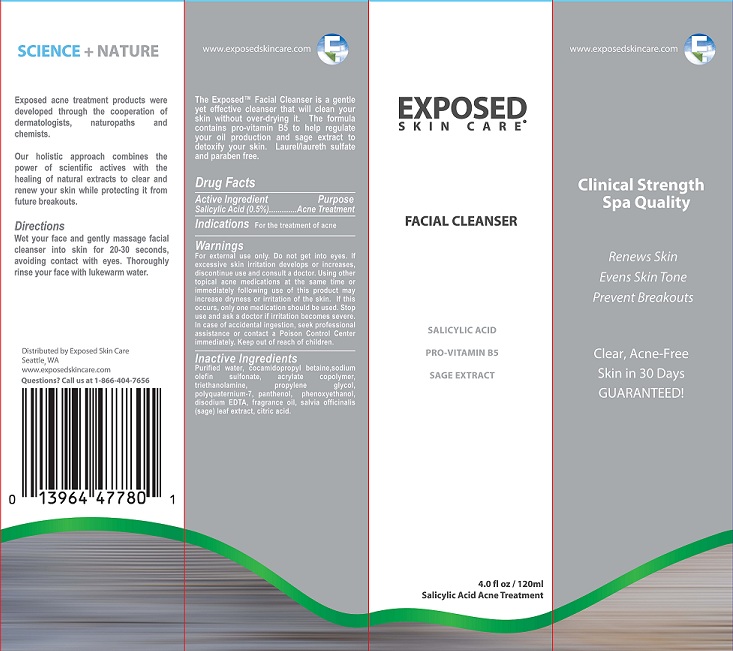 DRUG LABEL: FACIAL CLEANSER
NDC: 55878-105 | Form: GEL
Manufacturer: Halogent, LLC (DBA Exposed Skin Care) 
Category: otc | Type: HUMAN OTC DRUG LABEL
Date: 20130313

ACTIVE INGREDIENTS: SALICYLIC ACID 0.5 g/100 mL
INACTIVE INGREDIENTS: WATER; COCAMIDOPROPYL BETAINE; SODIUM C18 OLEFIN SULFONATE; CARBOMER INTERPOLYMER TYPE A (ALLYL SUCROSE CROSSLINKED); TROLAMINE; PROPYLENE GLYCOL; POLYQUATERNIUM-7 (70/30 ACRYLAMIDE/DADMAC; 1600 KD); PANTHENOL; PHENOXYETHANOL; EDETATE DISODIUM; SALVIA OFFICINALIS FLOWERING TOP; ANHYDROUS CITRIC ACID

PURPOSE

ACNE TREATMENT

ACTIVE INGREDIENT

SALICYLIC ACID (0.5%)

WARNINGS FOR EXTERNAL USE ONLY

USE

FOR THE TREATMENT OF ACNE

Ask a doctor or pharmacist before use if you are using other topical acne medications at the same time or immediately following use of this product. This may increase dryness or irritation of the skin. If this occurs, only one medication should be used unless directed by a doctor.

Keep out of reach of children. If swallowed, get medical help or contact a Poison Control Center right away.

When using this product avoid contact with eyes. If contact occurs, flush thoroughly with water.

Directions

Wet your face and gently massage facial cleanser into skin for 10 - 15 seconds, avoiding contact with eyes. Thoroughly rinse your face with lukewarm water.

- Wash the entire affected area one to three times daily.
- Because excessive drying of the skin may occur, start with one application daily, then gradually increase to two or three times daily if needed or as directed by a doctor
- If bothersome dryness or peeling occurs, reduce application to once a day or every other day.

Inactive Ingredients

Water, cocamidopropyl betaine, sodium olefin sulfonate, acrylate copolymer, triethanolamine, propylene glycol, polyquaternium-7, panthenol, phenoxyethanol, disodium EDTA, salvia officinalis (sage) leaf extract, citric acid, fragrance.

Questions?

1-866-404-7656 or www.exposedskincare.com